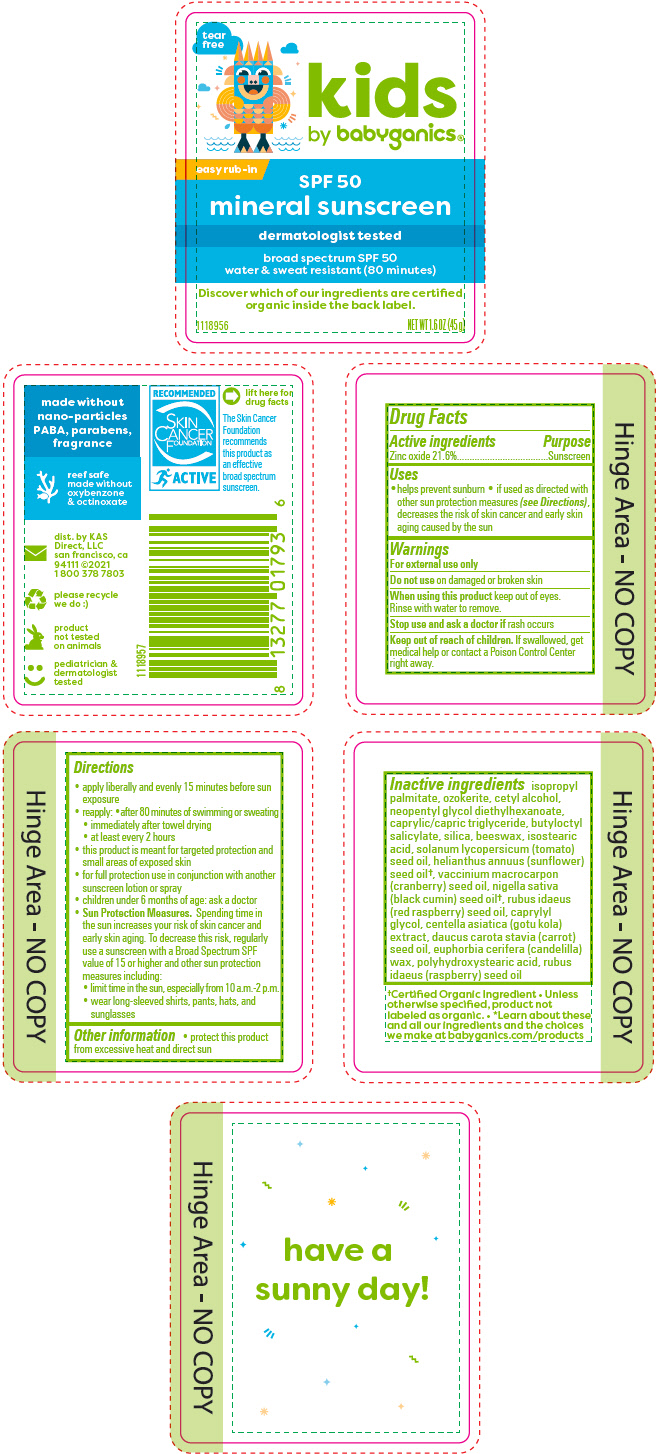 DRUG LABEL: SPF 50 Mineral Sunscreen 
NDC: 59062-2201 | Form: STICK
Manufacturer: KAS Direct LLC dba BabyGanics
Category: otc | Type: HUMAN OTC DRUG LABEL
Date: 20251205

ACTIVE INGREDIENTS: Zinc Oxide 216 mg/1 g
INACTIVE INGREDIENTS: YELLOW WAX; BUTYLENE GLYCOL; BUTYLOCTYL SALICYLATE; MEDIUM-CHAIN TRIGLYCERIDES; CAPRYLYL GLYCOL; CENTELLA ASIATICA WHOLE; CETYL ALCOHOL; CARROT SEED OIL; CANDELILLA WAX; ISOPROPYL PALMITATE; ISOSTEARIC ACID; NEOPENTYL GLYCOL DIETHYLHEXANOATE; CERESIN; POLYHYDROXYSTEARIC ACID (2300 MW); SILICON DIOXIDE; NIGELLA SATIVA SEED OIL; RASPBERRY SEED OIL; CRANBERRY SEED OIL; SUNFLOWER OIL; Water; TOMATO SEED OIL

SPF 50 Mineral Sunscreen Stick
bkids

Drug Facts

Active ingredients

Zinc oxide 21.6%

Purpose

Sunscreen

Uses

- helps prevent sunburn
- if used as directed with other sun protection measures (see Directions), decreases the risk of skin cancer and early skin aging caused by the sun

Warnings

For external use only

Do not use on damaged or broken skin

When using this product keep out of eyes. Rinse with water to remove.

Stop use and ask a doctor if rash occurs

Keep out of reach of children. If swallowed, get medical help or contact a Poison Control Center right away.

Directions

- apply liberally and evenly 15 minutes before sun exposure
- reapply:
  - after 80 minutes of swimming or sweating
  - immediately after towel drying
  - at least every 2 hours
- this product is meant for targeted protection and small areas of exposed skin
- for full protection use in conjunction with another sunscreen lotion or spray
- children under 6 months of age: ask a doctor
- Sun Protection Measures. Spending time in the sun increases your risk of skin cancer and early skin aging. To decrease this risk, regularly use a sunscreen with a Broad Spectrum SPF value of 15 or higher and other sun protection measures including:
  - limit time in the sun, especially from 10 a.m.-2 p.m.
  - wear long-sleeved shirts, pants, hats, and sunglasses

Other information

- protect this product from excessive heat and direct sun

Inactive ingredients

isopropyl palmitate, ozokerite, cetyl alcohol, neopentyl glycol diethylhexanoate, caprylic/capric triglyceride, butyloctyl salicylate, silica, beeswax, isostearic acid, solanum lycopersicum (tomato) seed oil, helianthus annuus (sunflower) seed oil [Certified Organic Ingredient • Unless otherwise specified, product not labeled as organic. • *Learn about these and all our ingredients and the choices we make at babyganics.com/products] , vaccinium macrocarpon (cranberry) seed oil, nigella sativa (black cumin) seed oil, rubus idaeus (red raspberry) seed oil, caprylyl glycol, centella asiatica (gotu kola) extract, daucus carota stavia (carrot) seed oil, euphorbia cerifera (candelilla) wax, polyhydroxystearic acid, rubus idaeus (raspberry) seed oil

dist. by KAS
Direct, LLC
san francisco, ca
94111

PRINCIPAL DISPLAY PANEL - 45 g Container Label

tear
free

kids
by babyganics®

easy rub-in

SPF 50
mineral sunscreen

dermatologist tested

broad spectrum SPF 50
water & sweat resistant (80 minutes)

Discover which of our ingredients are certified
organic inside the back label.

1118956
NET WT 1.6 OZ (45 g)